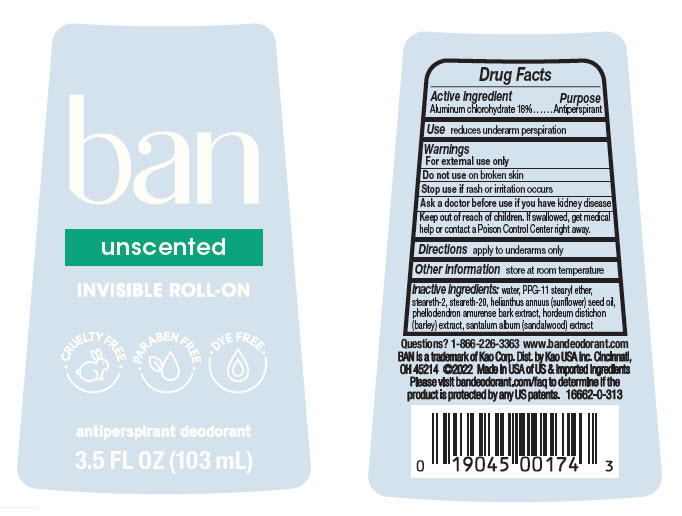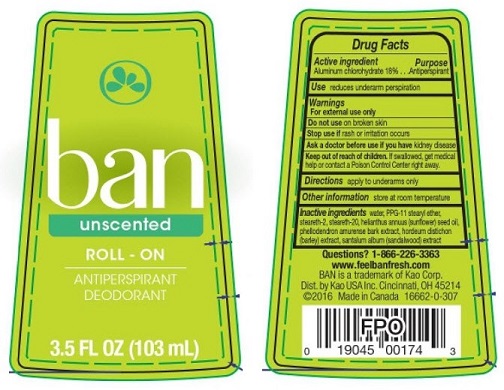 DRUG LABEL: Ban
NDC: 10596-338 | Form: LIQUID
Manufacturer: Kao USA Inc.
Category: otc | Type: HUMAN OTC DRUG LABEL
Date: 20250101

ACTIVE INGREDIENTS: ALUMINUM CHLOROHYDRATE 20 g/103 mL
INACTIVE INGREDIENTS: WATER; STEARETH-2; STEARETH-20; SANDALWOOD; PHELLODENDRON AMURENSE BARK; BARLEY; PPG-11 STEARYL ETHER; SUNFLOWER OIL

Ban Roll-On Antiperspirant Deodorant Unscented

Drug Facts

Active ingredient

Aluminum chlorohydrate 18%

Purpose

Antiperspirant

Use

reduces underarm perspiration

Warnings

For external use only

Do not use on broken skin

Stop use if rash or irritation occurs

Ask a doctor before use if you have kidney disease

Keep out of reach of children. If swallowed, get medical help or contact a Poison Control Center right away.

Directions

apply to underarms only

Other information

store at room temperature

Inactive ingredients

water, PPG-11 stearyl ether, steareth-2, steareth-20, helianthus annuus (sunflower) seed oil, phellodendron amurense bark extract, hordeum distichon (barley) extract, santalum album (sandalwood) extract

Questions? 1-866-226-3363

www.feelbanfresh.com

BAN is a trademark of Kao Corp.

Dist. by Kao USA Inc. Cincinnati, OH 45214

©2016 Made in Canada

CANADA MFD LABEL

ban

unscented
ROLL-ON

ANTIPERSPIRANT

DEODORANT

3.5 FL OZ (103 mL)

USA MANUFACTURED LABEL

ban

unscented
INVISIBLE ROLL-ON

antiperspirant deodorant

3.5 FL OZ (103 mL)